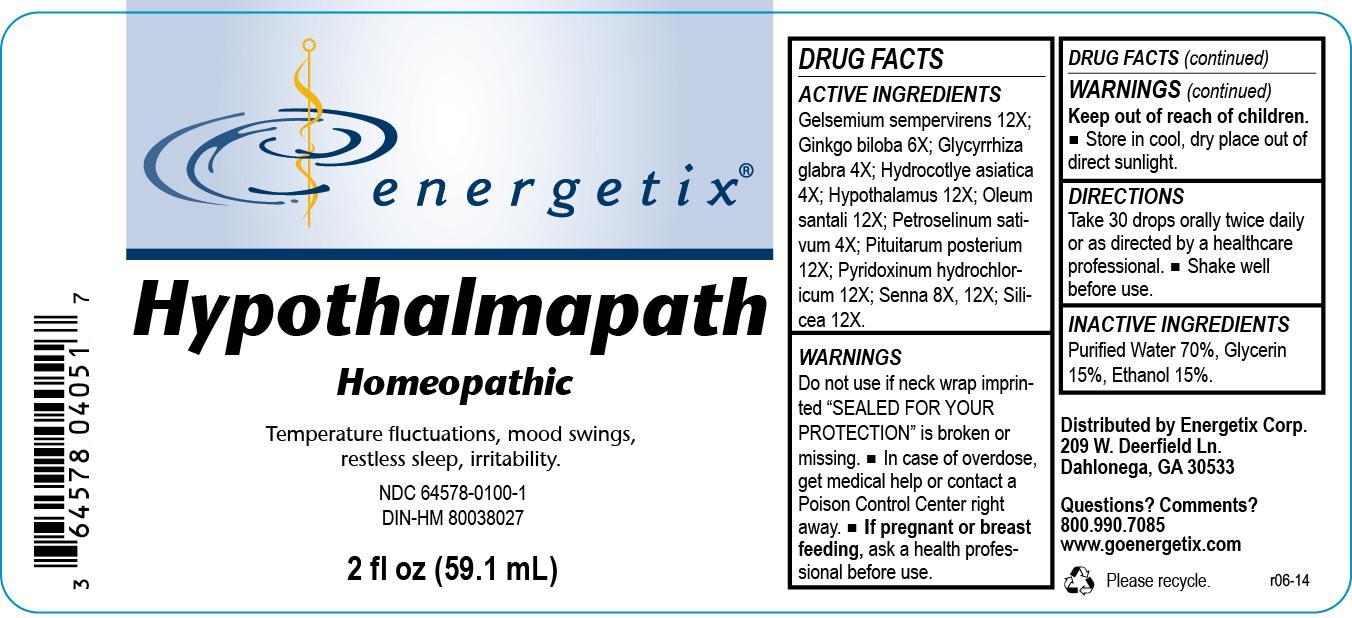 DRUG LABEL: Hypothalmapath
NDC: 64578-0100 | Form: LIQUID
Manufacturer: Energetix Corp
Category: homeopathic | Type: HUMAN OTC DRUG LABEL
Date: 20140204

ACTIVE INGREDIENTS: GELSEMIUM SEMPERVIRENS ROOT 12 [hp_X]/59.1 mL; GINKGO 6 [hp_X]/59.1 mL; GLYCYRRHIZA GLABRA 4 [hp_X]/59.1 mL; CENTELLA ASIATICA 4 [hp_X]/59.1 mL; BOS TAURUS HYPOTHALAMUS 12 [hp_X]/59.1 mL; SANDALWOOD OIL 12 [hp_X]/59.1 mL; PETROSELINUM CRISPUM 4 [hp_X]/59.1 mL; SUS SCROFA PITUITARY GLAND 12 [hp_X]/59.1 mL; PYRIDOXINE HYDROCHLORIDE 12 [hp_X]/59.1 mL; SENNA LEAF 8 [hp_X]/59.1 mL; SILICON DIOXIDE 12 [hp_X]/59.1 mL
INACTIVE INGREDIENTS: water 41.356555 mL/59.1 mL; ALCOHOL 8.862119 mL/59.1 mL; GLYCERIN 8.862119 mL/59.1 mL

Hypothalmapath

Active Ingredients

Gelsemium sempervirens 12X; Ginkgo biloba 6X; Glycyrrhiza glabra 4X; Hydrocotlye asiatica 4X; Hypothalamus 12X; Oleum santali 12X; Petroselinum sativum 4X; Pituitarum posterium 12X; Pyridoxinum hydrochloricum 12X; Senna 8X, 12X; Silicea 12X

Do not use if neck wrap imprinted "SEALED FOR YOUR PROTECTION" is broken or missing.

OVERDOSAGE

In case of overdose, get medical help or contact a Poison Control Center right away.

PREGNANCY OR BREAST FEEDING

If pregnant or breast feeding, ask a health professional before use.

Keep out of reach of children.

STORAGE AND HANDLING

Store in cool, dry place out of direct sunlight.

Questions? Comments?

800.990.7085 www.goenergetix.com

PURPOSE

Temperature fluctuations, mood swings, restless sleep, irritability.

INACTIVE INGREDIENT

Purified Water 70%, Glycerin 15%, Ethanol 15%.

DOSAGE AND ADMINISTRATION

Take 30 drops orally twice daily or as directed by a healthcare professional. Shake well before use.

INDICATIONS AND USAGE

Temperature fluctuations, mood swings, restless sleep, irritability.